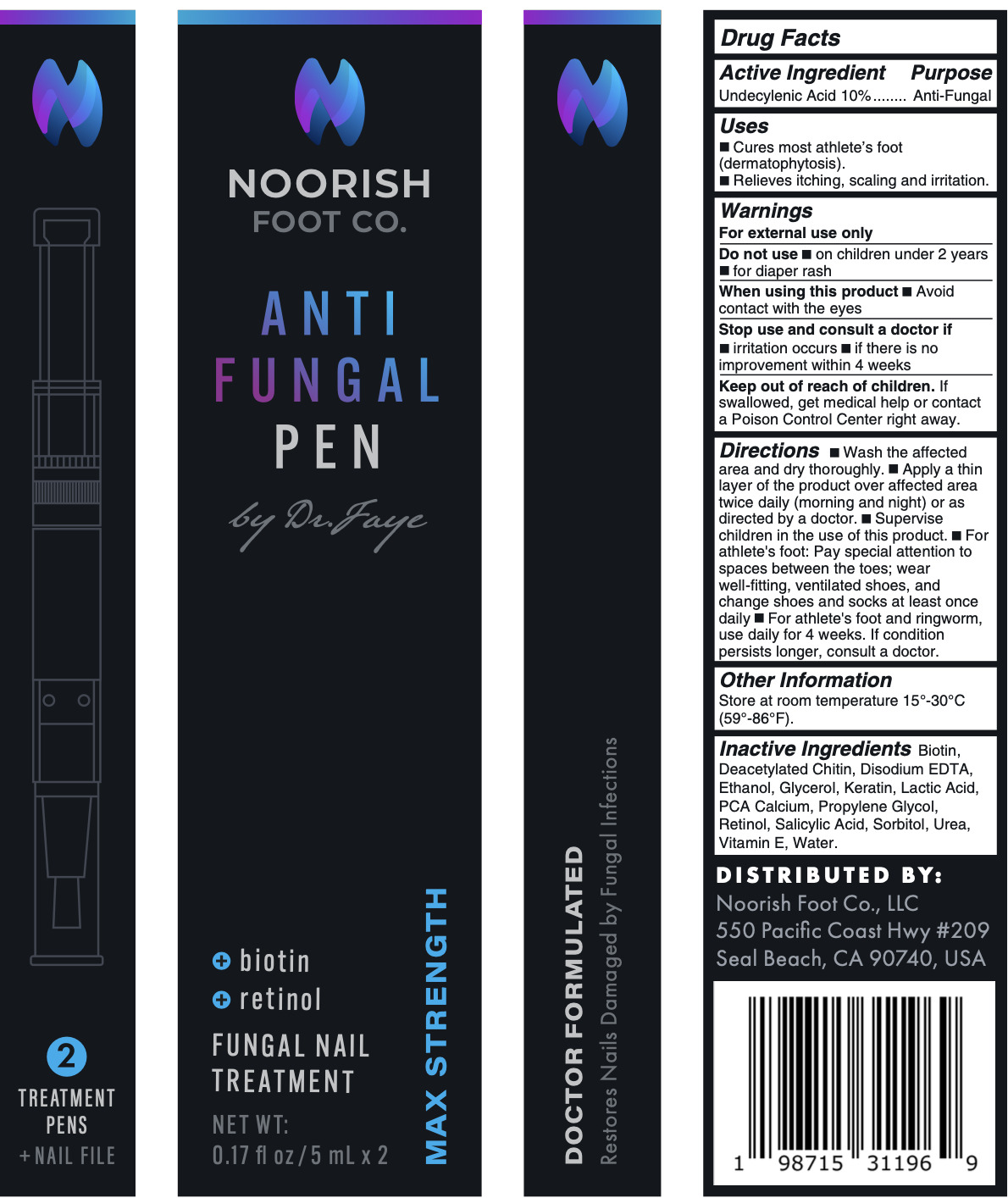 DRUG LABEL: Noorish Foot Co. Anti-Fungal Pen
NDC: 84841-111 | Form: LIQUID
Manufacturer: Noorish Foot Co. LLC
Category: otc | Type: HUMAN OTC DRUG LABEL
Date: 20251117

ACTIVE INGREDIENTS: UNDECYLENIC ACID 10 mg/100 mL
INACTIVE INGREDIENTS: ALPHA-TOCOPHEROL; WATER; SALICYLIC ACID; GLYCERIN; LACTIC ACID; SORBITOL; CHITIN; UREA; RETINOL; PROPYLENE GLYCOL; EDETATE DISODIUM; ACETALDEHYDE; CALCIUM PCA; BIOTIN; KERATIN, TYPE I CYTOSKELETAL 18

Noorish Anti-Fungal Pen 5mL

Active Ingredient(s)

Undecylenic Acid 10%........ Anti-Fungal

Purpose

Anti-Fungal

Use

Cures most athlete's foot (dermatophytosis).
Relieves itching, scaling and

Warnings

For external use only

Do not use on • children under 2 years

• for diaper rash

When using this product • Avoid contact with the eyes

Stop use and consult a doctor if

• irritation occurs • if there is no improvement within 4 weeks

Keep out of reach of children. If swallowed, get medical help or contact a Poison Control Center right away.

Directions

• Wash the affected area and dry thoroughly. • Apply a thin layer of the product over the affected area twice daily (morning and night) or as directed by a doctor. • Supervise children in the use of this product. • For athlete's foot: Pay special attention to spaces between the toes; wear well-fitting, ventilated shoes, and change shoes and socks at least once daily • For athlete's foot and ringworm, use daily for 4 weeks. If the condition persists longer, consult a doctor.

Other information

Store at room temperature 15°-30°C (59°-86°F).

Inactive ingredients

Biotin, Deacetylated Chitin, Disodium EDTA,

Ethanol, Glycerol, Keratin, Lactic Acid,

PCA Calcium, Propylene Glycol, Retinol, Salicylic Acid, Sorbitol, Urea,

Vitamin E, Water.

Package Label - Principal Display Panel

5 mL: NDC: 84841-111-11